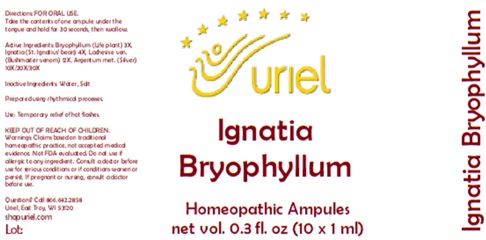 DRUG LABEL: Ignatia Bryophyllum
NDC: 48951-5068 | Form: LIQUID
Manufacturer: Uriel Pharmacy Inc.
Category: homeopathic | Type: HUMAN OTC DRUG LABEL
Date: 20250125

ACTIVE INGREDIENTS: KALANCHOE DAIGREMONTIANA LEAF 3 [hp_X]/1 mL; STRYCHNOS IGNATII SEED 4 [hp_X]/1 mL; SILVER 10 [hp_X]/1 mL; LACHESIS MUTA VENOM 12 [hp_X]/1 mL
INACTIVE INGREDIENTS: WATER; SODIUM CHLORIDE

Ignatia Bryophyllum

INDICATIONS AND USAGE

Directions: FOR ORAL USE.

DOSAGE AND ADMINISTRATION

Take the contents of one ampule under the tongue and hold for 30 seconds, then swallow.

ACTIVE INGREDIENT

Active Ingredients: Bryophyllum (Life plant) 3X, Ignatia (St. Ignatius’ bean) 4X, Lachesis e ven. (Bushmaster venom) 12X, Argentum met. (Silver) 10X/20X/30X

Inactive Ingredients: Water, Salt

Prepared using rhythmical processes.

PURPOSE

Use: Temporary relief of hot flashes.

KEEP OUT OF REACH OF CHILDREN.

WARNINGS

Warnings: Claims based on traditional homeopathic practice, not accepted medical evidence. Not FDA evaluated. Do not use if allergic to any ingredient. Consult a doctor before use for serious conditions or if conditions worsen or persist. If pregnant or nursing, consult a doctor before use.

Questions? Call 866.642.2858
Uriel, East Troy, WI 53120
shopuriel.com

Lot: